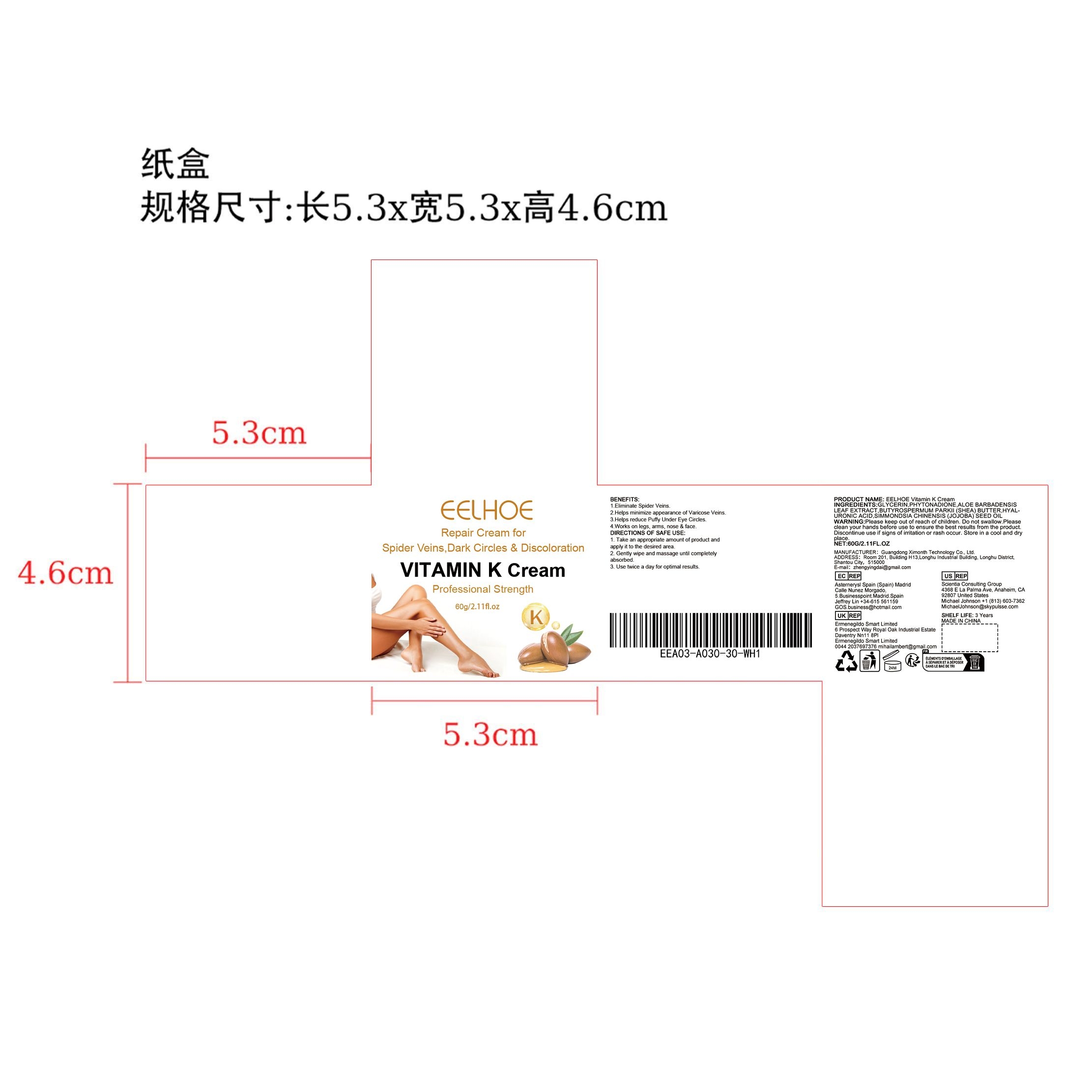 DRUG LABEL: EELHOE Vitamin K Cream
NDC: 84660-031 | Form: CREAM
Manufacturer: Guangdong Ximonth Technology Co., Ltd.
Category: otc | Type: HUMAN OTC DRUG LABEL
Date: 20240926

ACTIVE INGREDIENTS: SHEA BUTTER 9 g/60 g; HYALURONIC ACID 18 g/60 g; ALOE VERA LEAF 9 g/60 g; JOJOBA OIL 6 g/60 g; PHYTONADIONE 6 g/60 g
INACTIVE INGREDIENTS: GLYCERIN 12 g/60 g

Active Ingredient(s)

PHYTONADIONE、ALOE BARBADENSIS LEAF EXTRACT、BUTYROSPERMUM PARKII (SHEA) BUTTER、HYALURONIC ACID、
SIMMONDSIA CHINENSIS (JOJOBA) SEED OIL

Purpose

Improves skin condition

Use

1. Take an appropriate amount of product and apply it to the desired area.
2. Gently wipe and massage until completely absorbed.
3. Use twice a day for optimal results.

Warnings

Please keep out of reach of children.Do not swallow.Please clean your hands before use to ensure the best results from the product.Discontinue use if signs of irritation or rash occur.Store in a cool and dry place.

Do not use

Discontinue use if signs of irritation or rash occur.

STOP USE

Discontinue use if signs of irritation or rash occur.

KEEP OUT OF REACH OF CHILDREN

Please keep out of reach of children. Do not swallow.

STORAGE AND HANDLING

Avoid freezing and excessive heat above 40C (104F) ）
Store in a cool and dry place.

INACTIVE INGREDIENT

GLYCERIN